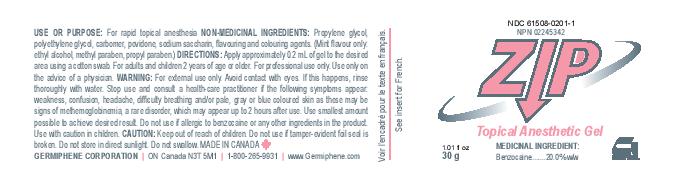 DRUG LABEL: Zip Topical Anesthetic Gel Strawberry
NDC: 61508-0202 | Form: GEL
Manufacturer: Germiphene Corporation
Category: otc | Type: HUMAN OTC DRUG LABEL
Date: 20170614

ACTIVE INGREDIENTS: BENZOCAINE 20 g/100 g
INACTIVE INGREDIENTS: FD&C RED NO. 40 0.002 g/100 g; PROPYLENE GLYCOL 43.7 g/100 g; POLYETHYLENE GLYCOL 400 30.75 g/100 g; POVIDONE 0.25 g/100 g; SACCHARIN SODIUM 0.7 g/100 g; CARBOMER 934 3.1 g/100 g

Zip Topical Anesthetic Gel Strawberry

INDICATIONS AND USAGE

For rapid topical anesthesia

PURPOSE

For rapid topical anesthesia

ACTIVE INGREDIENT

Medicinal Ingredients: Benzocaine 20% w/w

INACTIVE INGREDIENT

Propylene glycol, polyethylene glycol, carbomer, povidone, sodium saccharin, flavouring and colouring agents. (mint flavour only: ethyl alcohol, methyl paraben, propyl paraben.)

DOSAGE AND ADMINISTRATION

Directions: Apply approximately 0.2 mL of gel to the desired area using a cotton swab. For adults and children 2 years of age or older. For professional useonly. Use only on the advice of a physician.

WARNINGS

Warning: For external use only. Avoid contact with eyes. If this happens, rinse thoroughly with water. Stop use and consult a health-care practitioner if the following symptoms appear: weakness, confusion, headache, difficulty breathing and/or pale, gray or blue coloured skin as these may be signs of methemoglobinemia, a rare disorder, which may appear up to 2 hours after use. Use smallest amount possible to achieve desired result. Do not use if allergic to benzocaine or any other ingredients in the product. Use with caution in children. Do not use if tamper-evident foil seal is broken. do not store in direct sunlight. Do not swallow.

Keep out of reach of children.